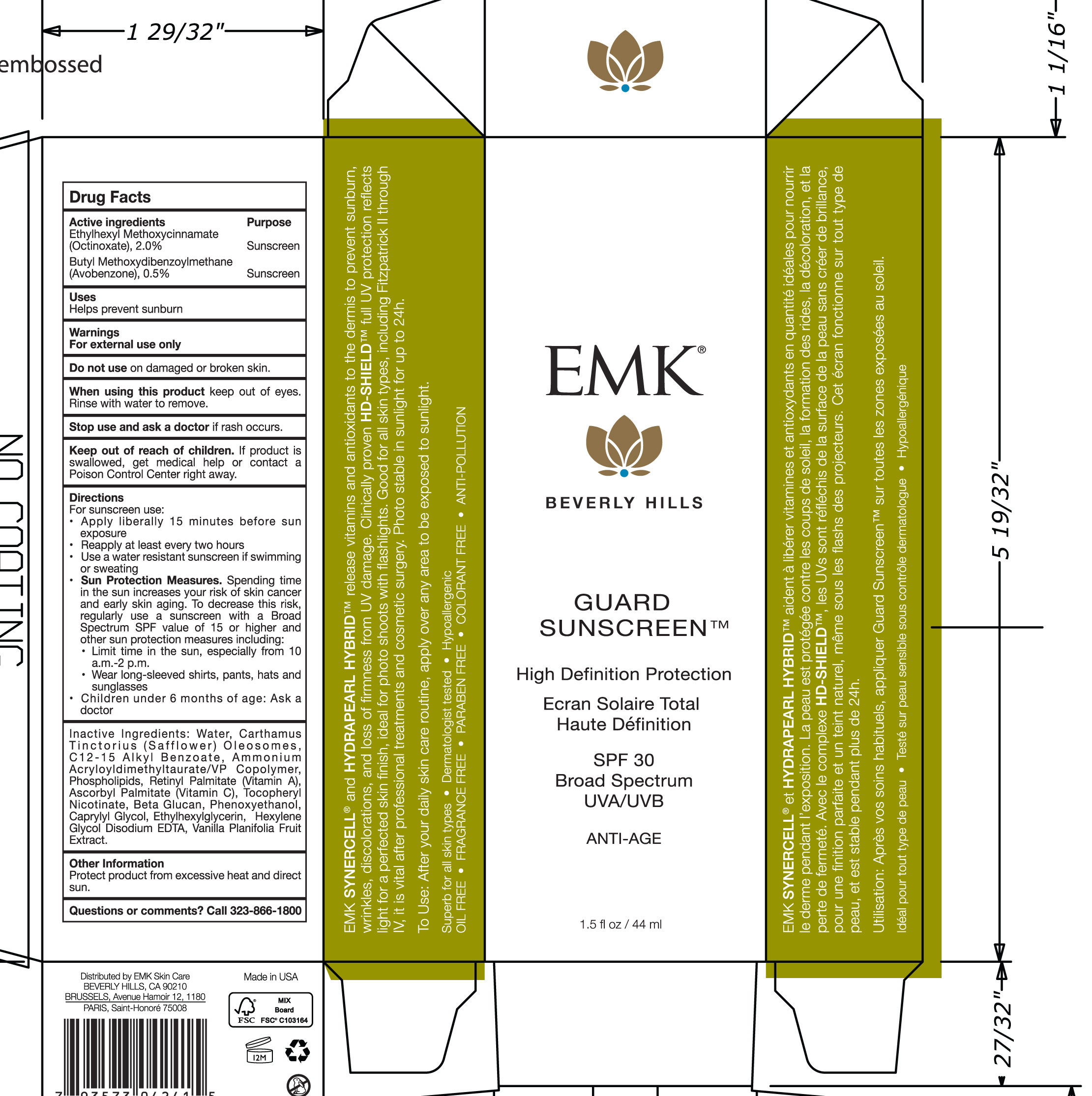 DRUG LABEL: Guard Sunscreen Broad Spectrum SPF 30
NDC: 56152-5008 | Form: LOTION
Manufacturer: COSMETIC ENTERPRISES LTD
Category: otc | Type: HUMAN OTC DRUG LABEL
Date: 20181220

ACTIVE INGREDIENTS: OCTINOXATE 2 g/100 mL; AVOBENZONE 0.5 g/100 mL
INACTIVE INGREDIENTS: CAPRYLYL GLYCOL; EDETATE DISODIUM; ASCORBYL PALMITATE; ETHYLHEXYLGLYCERIN; HEXYLENE GLYCOL; TOCOPHERYL NICOTINATE, D-.ALPHA.; VANILLA; PHENOXYETHANOL; WATER; CARTHAMUS TINCTORIUS SEED OLEOSOMES; ALKYL (C12-15) BENZOATE; AMMONIUM ACRYLOYLDIMETHYLTAURATE/VP COPOLYMER; LECITHIN, SOYBEAN; VITAMIN A PALMITATE

Guard Sunscreen High Defitinition Protection SPF 30

Active ingredients Purpose

Ethylhexylmethoxycinnamate (Octinoxate) 2.0% Sunscreen

ButylMethoxydibenzoylmethane (avobenzone) .5% Sunscreen

Uses

Helps Prevent Sunburn

Keep out of reach of children. If product is swallowed, get medical help or contact a Poison Control Center right away.

Stop use and ask a doctor if rash occurs.

Warnings

For External use only.

Do Not use on damaged or broken skin.

When using this product keep out of eyes. Rinse with water to remove.

Directions

For Sunscreen use:

- Aply liberally 15 minutes before sun exposure
- Reapply at least every 2 hours
- use a water resistant sunscreen if swimming or sweating
- Sun Protection measures.Spending time in the sun increases your risk of skin cancer and early skin aging. To decrease this risk, regularly use a sunscreen with a Broad Spectrum SPF value of 15 or higher and other sun protection measures including:
- Limit time in the sun, especially from 10 a.m. -2 p.m.
- Wear long-sleeved shirts, pants, hats, and sunglasses
- Children under 6 months of age: Ask a doctor

INACTIVE INGREDIENT

Inactive ingredients: Water, Carthamus Tinctorius (Safflower) Oleosomes, C12-15 Alkyl Benzoate, Ammonium Acryloyldimethyltaurate/VP Copolymer, Phospholipids, Retinyl Palmitate (Vitamin A), Ascorbyl Palmitate (Vitamin C), Tocopheryl Nicotinate, Beta Glucan, Phenoxyethanol, Caprylyl Glycol, Ethylhexylglycerin, Hexylene Glycol, Disodium EDTA, Vanilla Planifola Fruit Extract

PACKAGE LABEL

Guard Sunscreen

High Definition Protection

Ecran Solaire Total

Haute Definition

SPF 30

Broad Spectrum UVA/UVB

Anti-age

1.5fl oz/ 44ml